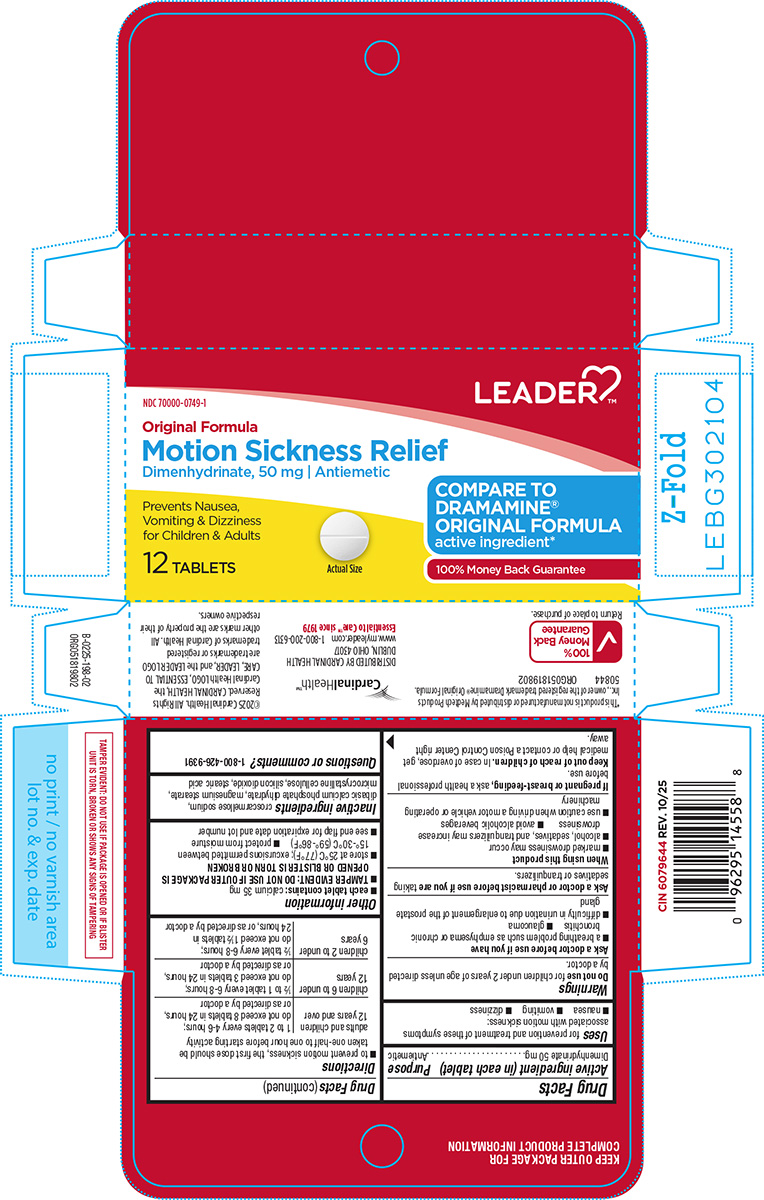 DRUG LABEL: Motion Sickness Relief
NDC: 70000-0749 | Form: TABLET
Manufacturer: Cardinal Health 110, LLC. DBA Leader
Category: otc | Type: HUMAN OTC DRUG LABEL
Date: 20251205

ACTIVE INGREDIENTS: DIMENHYDRINATE 50 mg/1 1
INACTIVE INGREDIENTS: CROSCARMELLOSE SODIUM; DIBASIC CALCIUM PHOSPHATE DIHYDRATE; MAGNESIUM STEARATE; MICROCRYSTALLINE CELLULOSE; SILICON DIOXIDE; STEARIC ACID

Leader 44-198

Active ingredient (in each tablet)

Dimenhydrinate 50 mg

Purpose

Antiemetic

Uses

for prevention and treatment of these symptoms associated with motion sickness:

- nausea
- vomiting
- dizziness

Warnings

Do not use

for children under 2 years of age unless directed by a doctor.

Ask a doctor before use if you have

- a breathing problem such as emphysema or chronic bronchitis
- glaucoma
- difficulty in urination due to enlargement of the prostate gland

Ask a doctor or pharmacist before use if you are

taking sedatives or tranquilizers.

When using this product

- marked drowsiness may occur
- avoid alcoholic beverages
- alcohol, sedatives, and tranquilizers may increase drowsiness
- use caution when driving a motor vehicle or operating machinery

If pregnant or breast-feeding,

ask a health professional before use.

Keep out of reach of children.

In case of overdose, get medical help or contact a Poison Control Center right away.

Directions

- to prevent motion sickness, the first dose should be taken one-half to one hour before starting activity

adults and children 12 years and over | 1 to 2 tablets every 4-6 hours; do not exceed 8 tablets in 24 hours, or as directed by a doctor
children 6 to under 12 years | ½ to 1 tablet every 6-8 hours; do not exceed 3 tablets in 24 hours, or as directed by a doctor
children 2 to under 6 years | ½ tablet every 6-8 hours; do not exceed 1½ tablets in 24 hours, or as directed by a doctor

Other information

- each tablet contains: calcium 35 mg
- see end flap for expiration date and lot number
- TAMPER EVIDENT: DO NOT USE IF OUTER PACKAGE IS OPENED OR BLISTER IS TORN OR BROKEN
- store at 25°C (77°F); excursions permitted between 15°-30°C (59°-86°F)
- protect from moisture

Inactive ingredients

croscarmellose sodium, dibasic calcium phosphate dihydrate, magnesium stearate, microcrystalline cellulose, silicon dioxide, stearic acid

Questions or comments?

1-800-426-9391

Principal display panel

NDC 70000-0749-1

LEADER™

Original Formula
Motion Sickness Relief

Dimenhydrinate, 50 mg | Antiemetic

Prevents Nausea,
Vomiting & Dizziness
for Children & Adults

12 TABLETS

Actual Size

COMPARE TO
DRAMAMINE®
ORIGINAL FORMULA
active ingredient*

100% Money Back Guarantee

TAMPER EVIDENT: DO NOT USE IF PACKAGE IS OPENED OR IF BLISTER
UNIT IS TORN, BROKEN OR SHOWS ANY SIGNS OF TAMPERING

*This product is not manufactured or distributed by Medtech Products
Inc., owner of the registered trademark Dramamine® Original Formula.
50844 ORG051819802

100%
Money Back
Guarantee
Return to place of purchase.

CardinalHealth™

DISTRIBUTED BY CARDINAL HEALTH
DUBLIN, OHIO 43017
www.myleader.com 1-800-200-6313
Essential to Care™ since 1979

©2025 Cardinal Health. All Rights
Reserved. CARDINAL HEALTH, the
Cardinal Health LOGO, ESSENTIAL TO
CARE, LEADER, and the LEADER LOGO
are trademarks or registered
trademarks of Cardinal Health. All
other marks are the property of their
respective owners.

Leader 44-198